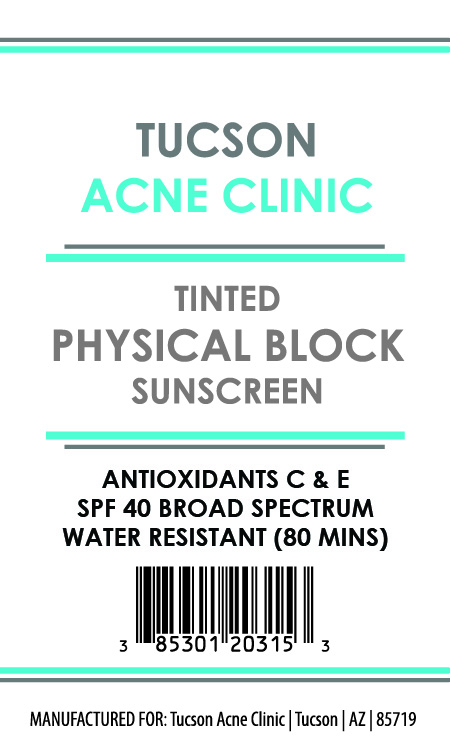 DRUG LABEL: Tinted Physical Block Sunscreen
NDC: 85301-203 | Form: CREAM
Manufacturer: Tucson Acne Clinic
Category: otc | Type: HUMAN OTC DRUG LABEL
Date: 20251209

ACTIVE INGREDIENTS: ZINC OXIDE 38 mg/1 g; TITANIUM DIOXIDE 80 mg/1 g
INACTIVE INGREDIENTS: DIMETHICONE CROSSPOLYMER; DIMETHICONE/VINYL DIMETHICONE CROSSPOLYMER (SOFT PARTICLE); DIMETHICONOL (2000 CST); CYCLOHEXASILOXANE; HYDROGEN DIMETHICONE (20 CST); LAURYL PEG/PPG-18/18 METHICONE; CI 77491; PEG-10 DIMETHICONE (600 CST); ALPHA-TOCOPHEROL ACETATE; DIMETHICONE; ALUMINA; CYCLOPENTASILOXANE; TETRAHEXYLDECYL ASCORBATE

Active Ingredients:

Titanium Dioxide 8% Zinc Oxide 3.8%

Purpose:

Sunscreen

Warning:

For External Use Only

Keep out of reach of children

Directions:

Apply liberally 15 minutes before sun exposure

INDICATIONS AND USAGE

For external use only

INACTIVE INGREDIENT

Alumina, Cyclohexasiloxane, Cyclopentasiloxane, Dimethicone, Dimethicone Crosspolymer, Dimethicone/Vinyl Dimethicone Crosspolymer, Dimethiconol, Iron Oxide (CI 77491), Lauryl PEG/PPG-18/18 Methicone, Hydrogen Dimethicone, PEG-10 Dimethicone, Tetrahexyldecyl Ascorbate, Tocopheryl Acetate

OTHER SAFETY INFORMATION

SAMPLE NOT FOR RESALE

keep out of reach of children